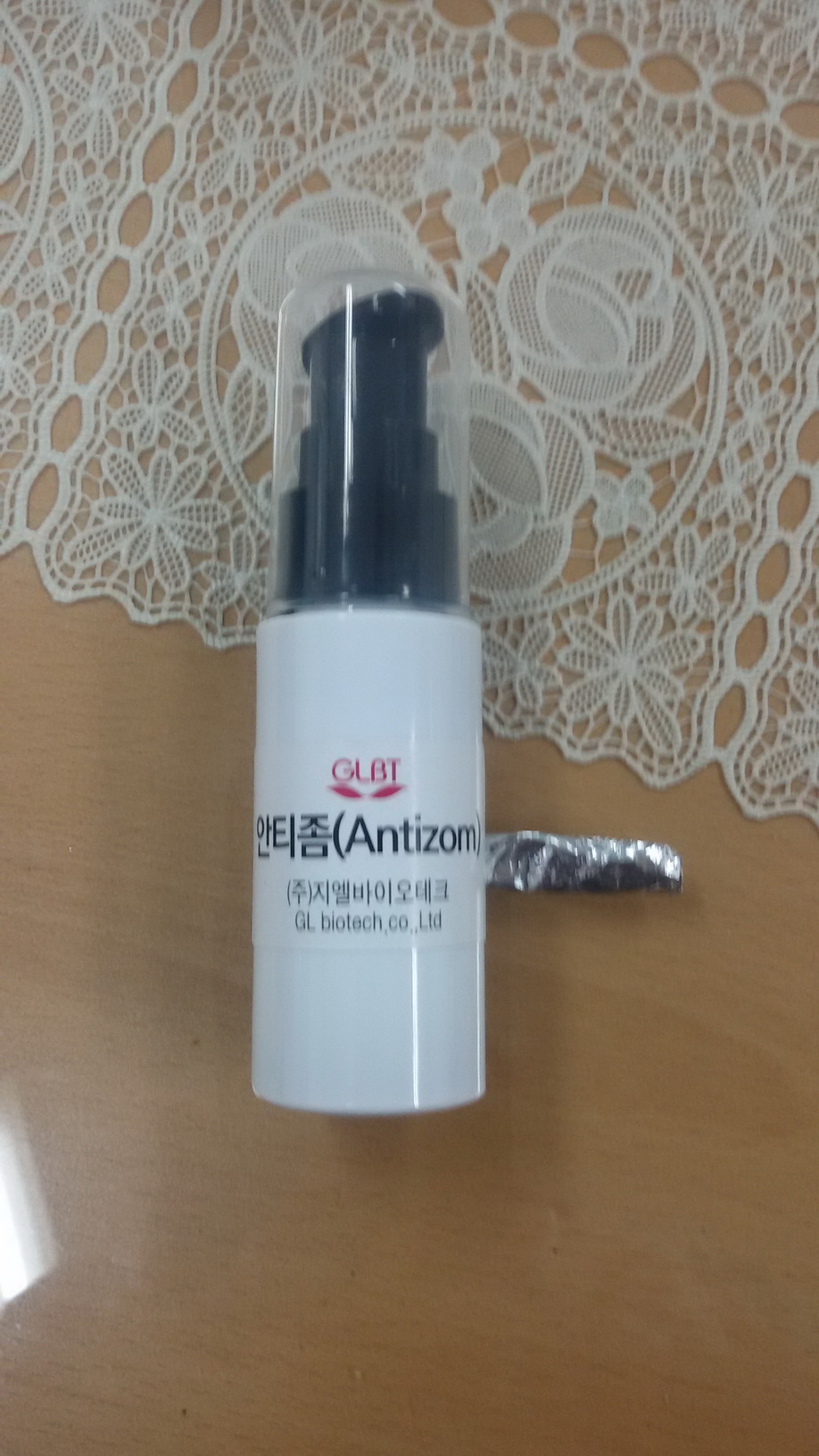 DRUG LABEL: Antizom
NDC: 69224-5001 | Form: LIQUID
Manufacturer: GL BioTech
Category: otc | Type: HUMAN OTC DRUG LABEL
Date: 20150910

ACTIVE INGREDIENTS: GLYCERIN 0.5 g/100 mL
INACTIVE INGREDIENTS: WATER; LAVENDER OIL

Drug Facts

ACTIVE INGREDIENT

glycerin

INACTIVE INGREDIENT

water, carbomer, ethanol, etc.

PURPOSE

to treat athlets's food of the nail

keep out of reach of the children

INDICATIONS AND USAGE

apply proper amount to the skin

WARNINGS

・Stop using the product when you have skin problems or the product disagrees with your skin
・Stop using the product immediately and consult a dermatologist if you have redness, swelling, itching or irritation on the skin while or after using the product.
・If the product gets into the eyes, don't rub but rinse with water.
・Don't place the product in any place where it will be subjected to extremely high or low temperatures or direct sunlight.

DOSAGE AND ADMINISTRATION

for external use only